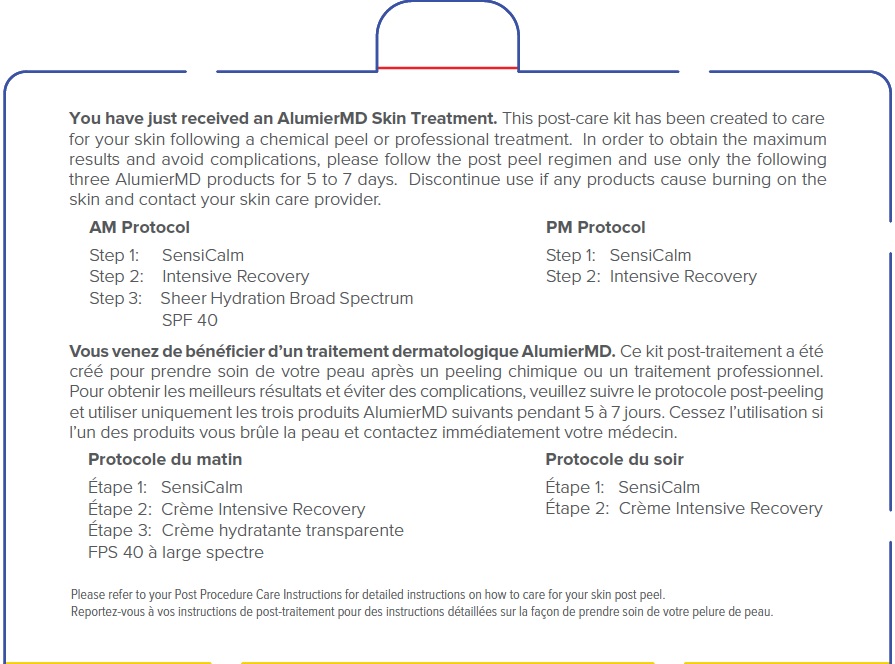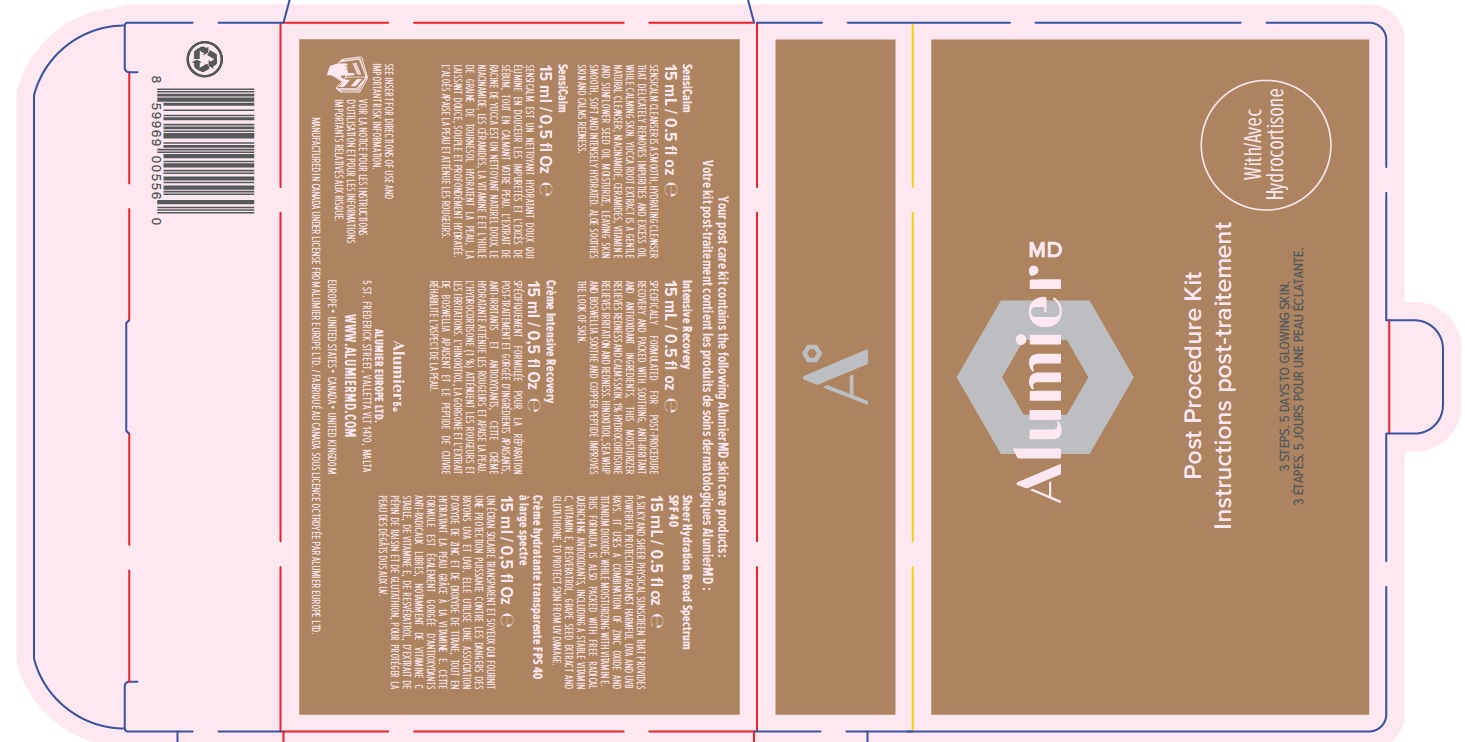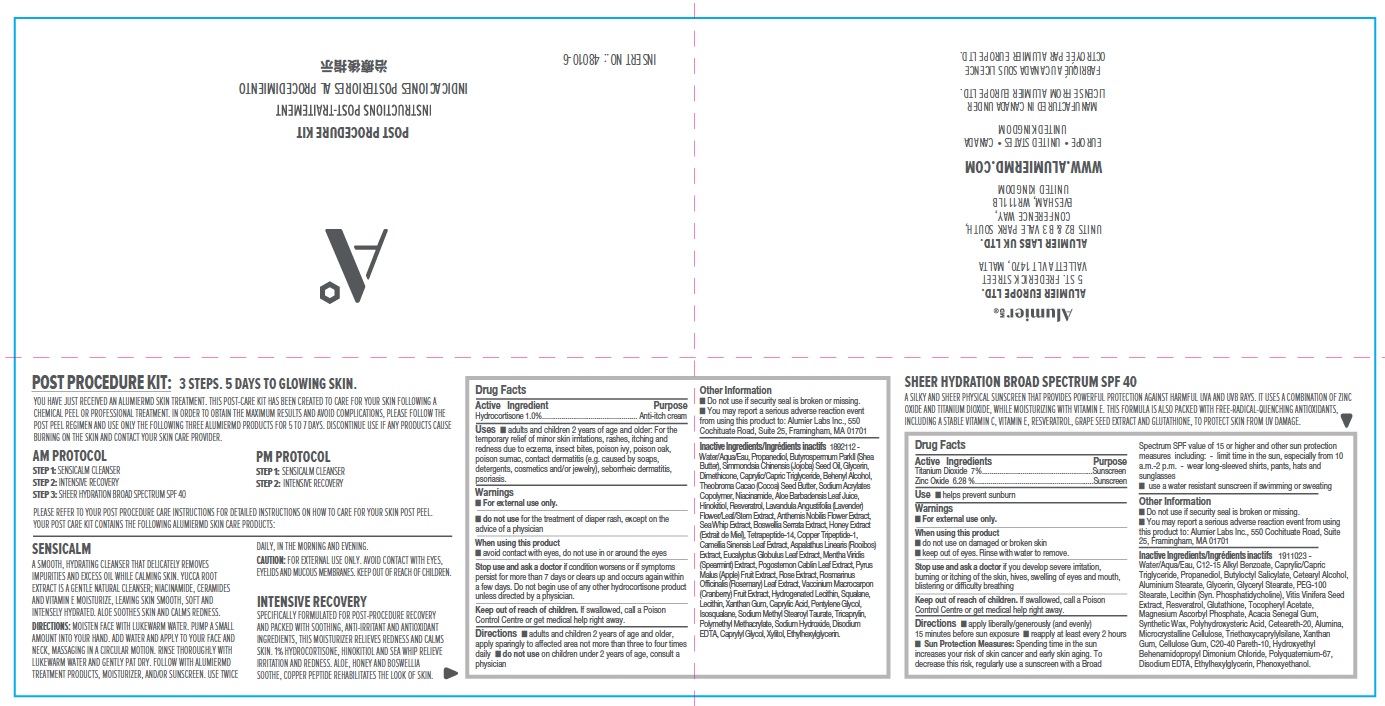 DRUG LABEL: Alumier MD Post Procedure Kit with Hydrocortisone
NDC: 69473-018 | Form: KIT | Route: TOPICAL
Manufacturer: Alumier Labs
Category: otc | Type: HUMAN OTC DRUG LABEL
Date: 20241202

ACTIVE INGREDIENTS: ZINC OXIDE 62.8 mg/1 mL; TITANIUM DIOXIDE 70 mg/1 mL; HYDROCORTISONE 10 mg/1 mL
INACTIVE INGREDIENTS: POLYHYDROXYSTEARIC ACID (2300 MW); ACACIA; LECITHIN, SOYBEAN; TRIETHOXYCAPRYLYLSILANE; WATER; GLYCERYL MONOSTEARATE; POLYOXYL 20 CETOSTEARYL ETHER; HYDROXYETHYL BEHENAMIDOPROPYL DIMONIUM CHLORIDE; MAGNESIUM ASCORBYL PHOSPHATE; C20-40 PARETH-10; BUTYLOCTYL SALICYLATE; GLYCERIN; VITIS VINIFERA SEED; ALUMINUM MONOSTEARATE; MEDIUM-CHAIN TRIGLYCERIDES; XANTHAN GUM; ALKYL (C12-15) BENZOATE; PROPANEDIOL; CARBOXYMETHYLCELLULOSE SODIUM, UNSPECIFIED FORM; .ALPHA.-TOCOPHEROL ACETATE; EDETATE DISODIUM; CETOSTEARYL ALCOHOL; PEG-100 STEARATE; ALUMINUM OXIDE; GLUTATHIONE; MICROCRYSTALLINE CELLULOSE; PHENOXYETHANOL; RESVERATROL; ETHYLHEXYLGLYCERIN; SYNTHETIC WAX (1800 MW); HONEY; EUCALYPTUS GLOBULUS LEAF; ALOE VERA LEAF; TRICAPRYLIN; ASPALATHUS LINEARIS WHOLE; .BETA.-THUJAPLICIN; LAVANDULA ANGUSTIFOLIA FLOWERING TOP; CHAMAEMELUM NOBILE FLOWER; PSEUDOPTEROGORGIA ELISABETHAE; APPLE; GREEN TEA LEAF; CRANBERRY; SQUALANE; ETHYLHEXYLGLYCERIN; JOJOBA OIL; DOCOSANOL; XANTHAN GUM; WATER; SHEA BUTTER; MEDIUM-CHAIN TRIGLYCERIDES; LECITHIN, SOYBEAN; DIMETHICONE; PROPANEDIOL; SODIUM METHYL STEAROYL TAURATE; NIACINAMIDE; RESVERATROL; INDIAN FRANKINCENSE; CAPRYLYL GLYCOL; PENTYLENE GLYCOL; MENTHA SPICATA; POLY(METHYL METHACRYLATE; 450000 MW); SODIUM HYDROXIDE; COCOA BUTTER; CAPRYLIC ACID; HYDROGENATED SOYBEAN LECITHIN; EDETATE DISODIUM; PREZATIDE COPPER; ROSEMARY; XYLITOL; GLYCERIN

Alumier MD Post Procedure Kit with Hydrocortisone

Active Ingredient

Hydrocortisone 1.0%

Purpose

Anti-itch cream

Uses

- adults and children 2 years of age and older: For the temporary relief of minor skin irritations, rashes, itching and redness due to eczema, insect bites, poison ivy, poison oak, poison sumac, contact dermatitis (e.g. caused by soaps, detergents, cosmetics and/or jewelry), seborrheic dermatitis, psoriasis.

Warnings

- For external use only

- do not use for the treatment of diaper rash, except on the advise of a physician

When using this product

- avoid contact with eyes, do not use in or around the eyes

Stop use and ask a doctor if condition worsens or if symptoms persist for more than 7 days or clears up and occurs again within a few days. Do not begin use of any other hydrocortisone product unless directed by a physician.

Keep out of reach of children. If swallowed, call a Poison Control Centre or get medical help right away.

Directions

- adults and children 2 years of age and older, apply sparingly to affected area not more than three to four times daily
- do not use on children under 2 years of age, consult a physician

Other Information

- Do not use if security seal is broken or missing.
- You may report a serious adverse reaction event from using this product to: Alumier Labs Inc., 550 Cochituate Road, Suite 25, Framingham, MA 01701

Inactive Ingredients

Water/Aqua/Eau, Butyrospermum Parkii (Shea Butter), Simmondsia Chinensis (Jojoba) Seed Oil, Glycerin, Dimethicone, Caprylic/Capric Triglyceride, Behenyl Alcohol, Theobroma Cacao (Cocoa) Seed Butter, Sodium Acrylates Copolymer, Niacinamide, Aloe Barbadensis Leaf Juice, Hinokitiol, Resveratrol, Lavandula Angustifolia (Lavender) Flower/Leaf/Stem Extract, Anthemis Nobilis Flower Extract, Sea Whip Extract, Boswellia Serrata Extract, Honey Extract (Extrait de Miel), Tetrapeptide-14, Copper Tripeptide-1, Camellia Sinensis Leaf Extract, Aspalathus Linearis (Rooibos) Extract, Eucalyptus Globulus Leaf Extract, Mentha Viridis (Spearmint) Extract, Pogostemon Cablin Leaf Extract, Pyrus Malus (Apple) Fruit Extract, Rose Extract, Rosmarinus Officinalis (Rosemary) Leaf Extract, Vaccinium Macrocarpon (Cranberry) Fruit Extract, Hydrogenated Lecithin, Squalane, Lecithin, Xanthan Gum, Caprylic Acid, Pentylene Glycol, Isosqualane, Sodium Methyl Stearoyl Taurate, Tricaprylin, Polymethyl Methacrylate, Sodium Hydroxide, Disodium EDTA, Caprylyl Glycol, Xylitol, Ethylhexylglycerin.

Active Ingredients

Titanium Dioxide 7%

Zinc Oxide 6.28%

Purpose

Sunscreen

Use

- helps prevent sunburn

Warnings

- For external use only

When using this product

- do not use on damaged or broken skin
- keep out of eyes. Rinse with water to remove.

Stop use and ask a doctor if you develop severe irritation, burning or itching of the skin, hives, swelling of eyes and mouth, blistering or difficulty breathing

Keep out of reach of children. If swallowed, call a Poison Control Centre or get medical help right away.

Directions

- apply liberally/generously (and evenly) 15 minutes before sun exposure
- reapply at least every 2 hours
- Sun Protection Measures: Spending time in the sun increases your risk of skin cancer and early skin aging. To decrease this risk, regularly use a sunscreen with a Broad Spectrum SPF value of 15 or higher and other sun protection measures including: - limit time in the sun, especially from 10 a.m. - 2 p.m. - wear long-sleeved shirts, pants, hats and sunglasses
- use a water resistant sunscreen if swimming or sweating

Other Information

- Do not use if security seal is broken or missing.
- You may report a serious adverse reaction event from using this product to: Alumier Labs Inc., Cochituate Road, Suite 25, Framingham, MA 01701

Inactive Ingredients

Water/Aqua/Eau, C12-15 Alkyl Benzoate, Caprylic/Capric Triglyceride, Propanediol, Butyloctyl Salicylate, Cetearyl Alcohol, Aluminium Stearate, Glycerin, Glyceryl Stearate, PEG-100 Stearate, Lecithin (Syn. Phosphatidycholine), Vitis Vinifera Seed Extract, Resveratrol, Glutathione, Tocopheryl Acetate, Magnesium Ascorbyl Phosphate, Acacia Senegal Gum, Synthetic Wax, Polyhydroxysteric Acid, Ceteareth-20, Alumina, Microcrystalline Cellulose, Triethoxycaprylylsilane, Xanthan Gum, Cellulose Gum, C20-4O Pareth-10, Hydroxyethyl Behenamidopropyl Dimonium Chloride, Polyquatemium-67, Disodium EDTA, Ethylhexylglycerin, Phenoxyethanol.

Company Information

Alumier MD

ALUMIER EUROPE LTD.

5 ST. FREDERICK STREET

VALLETTA VLT 1470, MALTA

WWW.ALUMIERMD.COM

EUROPE • UNITED STATES • CANADA • UNITED KINGDOM

MANUFACTURED IN CANADA UNDER LICENSE FROM ALUMIER EUROPE LTD.